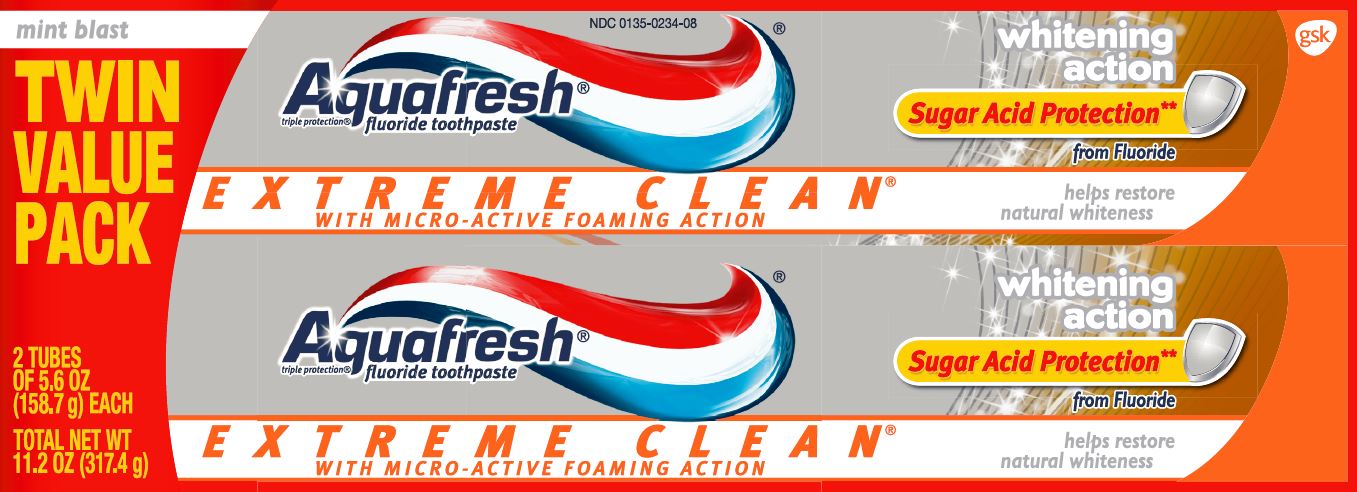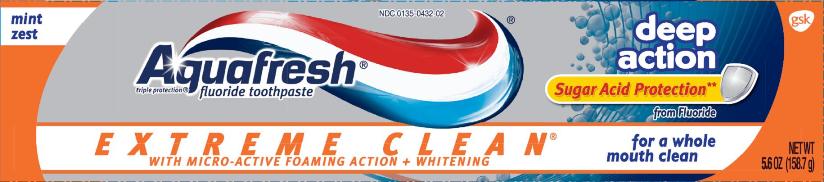 DRUG LABEL: AQUAFRESH

NDC: 0135-0234 | Form: PASTE
Manufacturer: Haleon US Holdings LLC
Category: otc | Type: HUMAN OTC DRUG LABEL
Date: 20260216

ACTIVE INGREDIENTS: SODIUM FLUORIDE 1.13 mg/1 g
INACTIVE INGREDIENTS: WATER; HYDRATED SILICA; SORBITOL; GLYCERIN; POLYETHYLENE GLYCOL 400; SODIUM LAURYL SULFATE; XANTHAN GUM; TITANIUM DIOXIDE; COCAMIDOPROPYL BETAINE; SACCHARIN SODIUM; D&C RED NO. 30

Drug Facts

Active ingredient

Sodium fluoride (0.15% w/v fluoride ion)

Purpose

Anticavity

Use

aids in the prevention of dental cavities

Warnings

When using this product,

if irritation occurs discontinue use

Keep out of reach of children under 6 years of age.

If you accidentally swallow more than used for brushing, get medical help or contact a Poison Control Center right away.

Keep out of reach of children under 6 years of age. (Whitening Multi Action only)

If more than used for brushing is accidentally swallowed, get medical help or contact a Poison Control Center right away.

Directions

- adults and children 2 years and older:
  - apply toothpaste onto a toothbrush
  - brush teeth thoroughly, preferably after each meal, or at least twice a day, and not more than 3 times a day, or as directed by a dentist or doctor. Minimize swallowing. Spit out after brushing.
  - to minimize swallowing for children under 6 years of age, use a pea-sized amount and supervise brushing and rinsing until good habits are established
- children under 2 yearsconsult a dentist or doctor

Other information

- store below 30°C (86°F)

Inactive ingredients (whitening action)

water, hydrated silica, sorbitol, glycerin, PEG-8, flavor, sodium lauryl sulfate, xanthan gum, titanium dioxide, cocamidopropyl betaine, sodium saccharin, synthetic iron oxide, red 30

Inactive ingredients (deep action)

water, hydrated silica, sorbitol, glycerin, PEG-8, sodium lauryl sulfate, flavor, xanthan gum, titanium dioxide, cocamidopropyl betaine, sodium saccharin, iron oxide, red 30

Questions or comments?

call toll-free 1-800-897-5623(English/Spanish) weekdays

Principal Display Panel

NDC 0135-0234-08

Aquafresh®

fluoride toothpaste

triple protection®

EXTREME CLEAN®

WITH MICRO-ACTIVE FOAMING ACTION

whitening action

Sugar Acid Protection**

from Fluoride

mint blast

helps restore natural whiteness

TWIN VALUE PACK

2 TUBES OF 5.6 OZ (158.7g) EACH

TOTAL NET WT 11.2 OZ (317.4g)

Aquafresh®Extreme Clean®Whitening Action toothpaste creates micro-active foam which seeks out hard to reach places in your mouth and fights bad breath. It rinses clear and carefully polishes your teeth so after only one tube you’ll be left with significantly cleaner, smoother, whiter teeth*. Take the Feeling of Clean to the Extreme!®

Sugar Acid Protection**

**With Sugar Acid Protection provided by fluoride, which strengthens enamel, creating a shield that protects the tooth surface against sugar acid attack.

triple protection

- healthy gums†
- strong teeth
- fresh breath

†with twice daily brushing

*vs a regular toothpaste

ALWAYS FOLLOW THE LABEL

Trademarks are owned by or licensed to the GSK group of companies.

AQUAFRESH, TRIPLE PROTECTION, the iconic Nurdle device are trademarks of the GSK group of companies.

GSKConsumer Healthcare

Warren, NJ 07059

©2015 GSK group of companies

1-800-897-5623

105517XA

Principal Display Panel

NDC 0135-0432-02

Aquafresh®

fluoride toothpaste

triple protection®

EXTREME CLEAN®

WITH MICRO-ACTIVE FOAMING ACTION + WHITENING

deep action

Sugar Acid Protection**

from Fluoride

mint zest

for a whole mouth clean

NET WT 5.6 oz (158.7g)

Aquafresh®Extreme Clean®Deep Action toothpaste creates micro-active foam which seeks hard to reach places; in between teeth and even the back of your tongue and rinses clear to leave your teeth clean and smooth. Enjoy a whole mouth clean. Take the Feeling of Clean to the Extreme!®

**With Sugar Acid Protection provided by fluoride, which strengthens enamel, creating a shield that protects the tooth surface against sugar acid attack.

healthy gums*

strong teeth

fresh breath

*with twice daily brushing

ALWAYS FOLLOW THE LABEL

AQUAFRESH, TRIPLE PROTECTION, the iconic Nurdle device are trademarks of the GSK group of companies.

GlaxoSmithKlineConsumer Healthcare, L.P.

Moon Township, PA 15108

©2015 GSK group of companies

We value your feedback

1-800-897-5623

101883XD